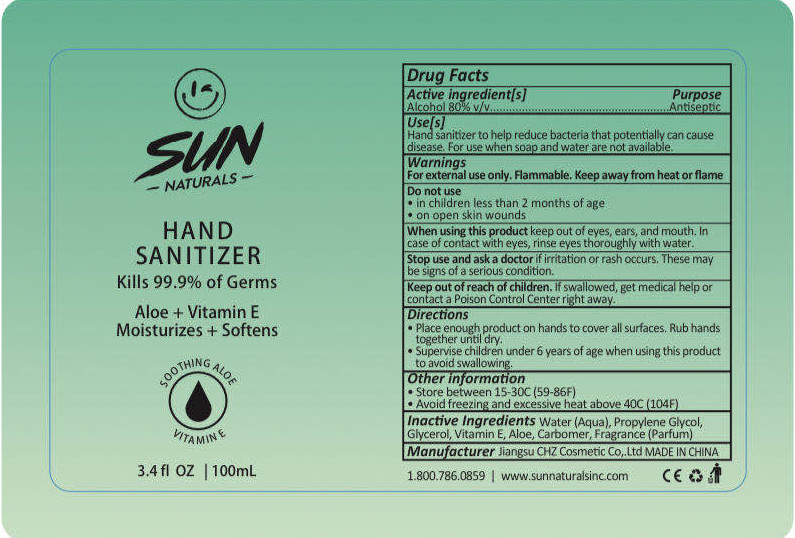 DRUG LABEL: Hand Sanitizer
NDC: 54284-003 | Form: LIQUID
Manufacturer: Jiangsu CHZ Cosmetic Co., Ltd.
Category: otc | Type: HUMAN OTC DRUG LABEL
Date: 20200507

ACTIVE INGREDIENTS: ALCOHOL 80 mL/100 mL
INACTIVE INGREDIENTS: GLYCERIN; ALOE; PROPYLENE GLYCOL; WATER; CARBOMER HOMOPOLYMER, UNSPECIFIED TYPE

PURPOSE

Disinfection
Sterilization

ACTIVE INGREDIENT

Alcohol

INACTIVE INGREDIENT

Water（Aqua）

Glycerol

Propylene Glycol

Aloe

Corbomer

keep out of reach of children

INDICATIONS AND USAGE

Place enough product on hands to cover all surfaces. Rub hands together until dry.

WARNINGS

For external use only. Flammable. Keep away from heat or flame

DOSAGE AND ADMINISTRATION

Disinfection
Sterilization
No Rinseing